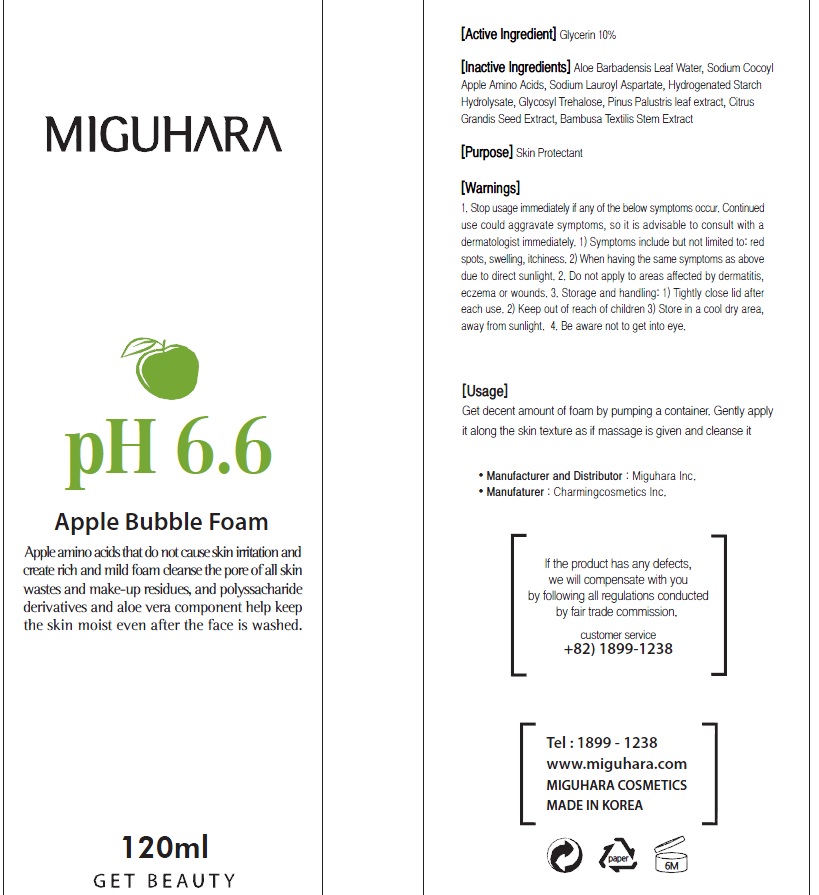 DRUG LABEL: Apple Bubble
NDC: 70380-130 | Form: INJECTABLE FOAM
Manufacturer: MIGUHARA
Category: otc | Type: HUMAN OTC DRUG LABEL
Date: 20160219

ACTIVE INGREDIENTS: Glycerin 12 g/120 mL
INACTIVE INGREDIENTS: ALOE VERA LEAF; Water

ACTIVE INGREDIENT

Active Ingredient: Glycerin 10.0%

INACTIVE INGREDIENT

Inactive Ingredients: Aloe Barbadensis Leaf Water, Sodium Cocoyl, Apple Amino Acids, Sodium Lauroyl Aspartate, Hydrogenated Starch Hydrolysate, Glycosyl Trehalose, Pinus Palustris leaf extract, Citrus Grandis Seed Extract, Bambusa Textilis Stem Extract

PURPOSE

Purpose: Skin Protectant

WARNINGS

1) Symptoms include but not limited to: red spots, swelling, itchiness. 2) When having the same symptoms as above due to direct sunlight. 2. Do not apply to areas affected by dermatitis, eczema or wounds. 3. Storage and handling: 1) Tightly close lid after each use. 2 Keep out of reach of children 3) Store in a cool dry area, away from sunlight 4. Be aware not to get into eye.

KEEP OUT OF REACH OF CHILDREN

Usage

Usage: Get decent amount of foam by pumping a container. Gently apply it along the skin texture as if massage is given and cleanse it.

Usage

Usage: Get decent amount of foam by pumping a container. Gently apply it along the skin texture as if massage is given and cleanse it.